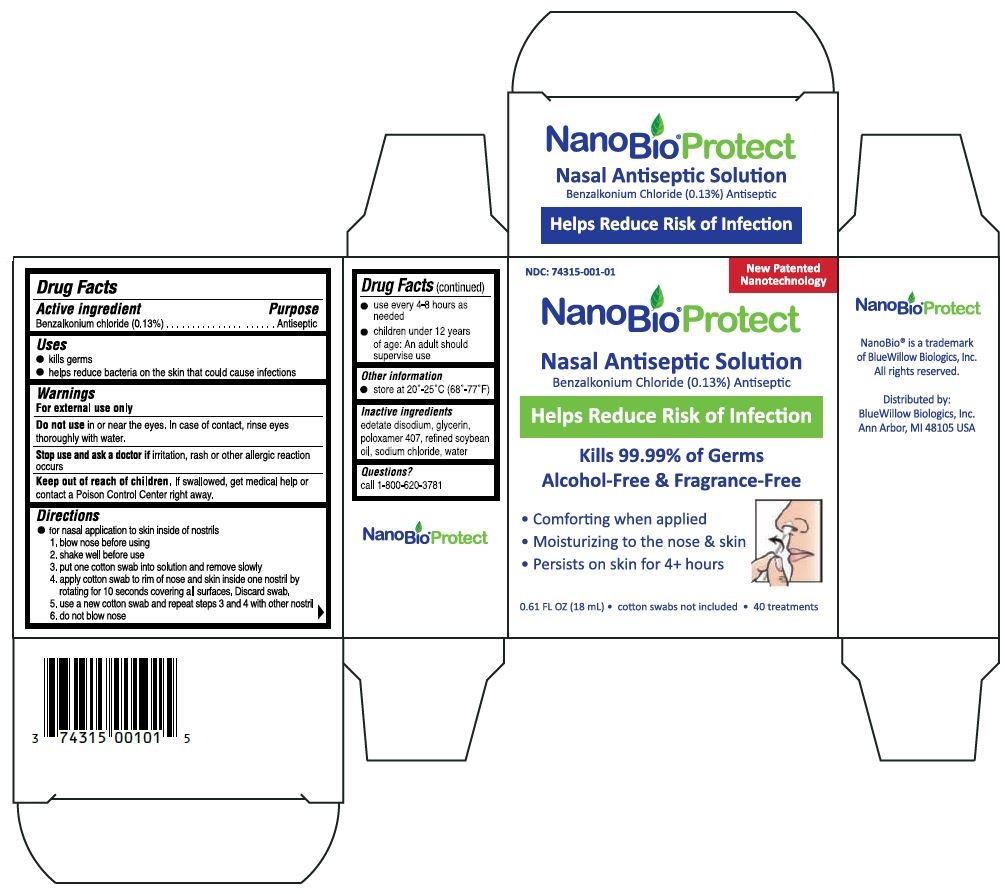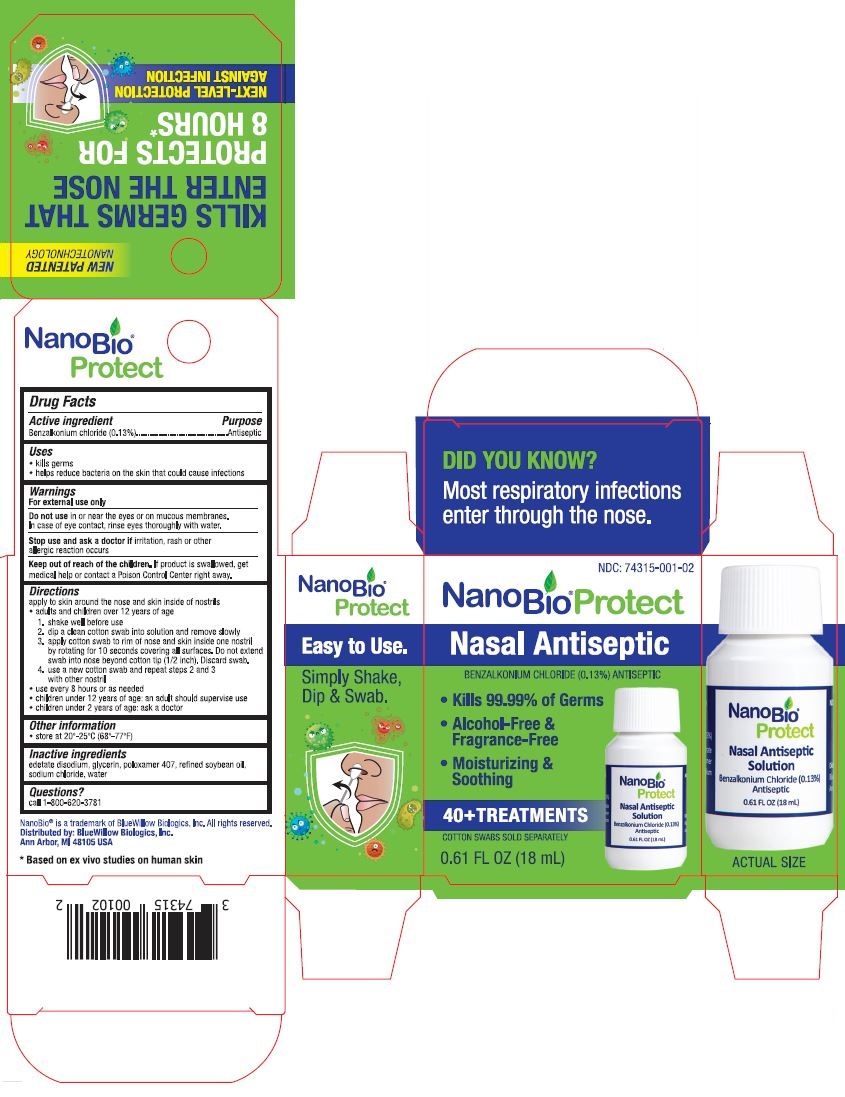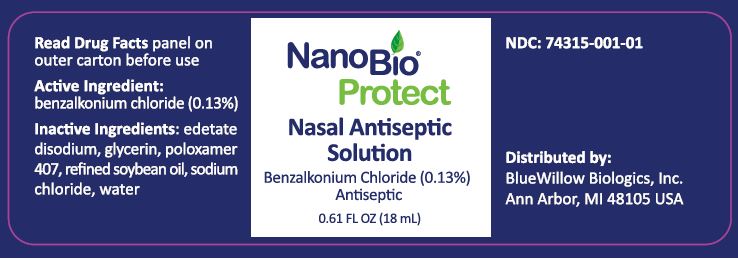 DRUG LABEL: NanoBio Protect Nasal Antiseptic Solution
NDC: 74315-001 | Form: SOLUTION
Manufacturer: BlueWillow Biologics, Inc.
Category: otc | Type: HUMAN OTC DRUG LABEL
Date: 20201009

ACTIVE INGREDIENTS: BENZALKONIUM CHLORIDE 0.0013 g/1 mL
INACTIVE INGREDIENTS: Edetate Disodium; Glycerin; Poloxamer 407; Soybean Oil; Sodium Chloride; Water

NanoBio®Protect Nasal Antiseptic Solution
Drug Facts

Active ingredient

Benzalkonium chloride (0.13%)

Purpose

Antiseptic

Uses

- kills germs
- helps reduce bacteria on the skin that could cause infections

Warnings
For external use only

Do not use in or near the eyes or on mucous membranes. In case of contact, rinse eyes thoroughly with water.

Stop use and ask a doctor if irritation, rash or other allergic reaction occurs

Keep out of reach of children. If product is swallowed, get medical help or contact a Poison Control Center right away.

Directions

apply to skin around the nose and skin inside of nostrils

- adults and children over 12 years of age
  1. shake well before use
  2. dip a clean cotton swab into solution and remove slowly
  3. apply cotton swab to rim of nose and skin inside one nostril by rotating for 10 seconds covering all surfaces. Do not extend swab into nose beyond cotton tip (1/2 inch). Discard swab.
  4. use a new cotton swab and repeat steps 2 and 3 with other nostril
- use every 8 hours as needed
- children under 12 years of age: an adult should supervise use
- children under 2 years of age: ask a doctor

Other information

- store at 20°-25°C (68° -77°F)

Inactive ingredients

edetate disodium, glycerin, poloxamer 407, refined soybean oil, sodium chloride, water

Questions?

call 1-800-620-3781

PRINCIPAL DISPLAY PANEL

NDC: 74315-001-01
New Patented Nanotechnology
NanoBio®Protect
Nasal Antiseptic Solution
Benzalkonium Chloride (0.13%) Antiseptic
Helps Reduce Risk of Infection
Kills 99.99% of Germs
Alcohol-Free & Fragrance-Free
● Comforting when applied
● Moisturizing to the nose & skin
● Persists on skin for 4+ hours
0.61 FL OZ (18 mL) ● cotton swabs not included ● 40 treatments
NanoBio®Protect
NanoBio® is a trademark of BlueWillow Biologics, Inc.
All rights reserved.
Distributed by:
BlueWillow Biologics, Inc.
Ann Arbor, MI 48105 USA

NDC: 74315-001-02
NanoBio® Protect
Nasal Antiseptic
BENZALKONIUM CHLORIDE (0.13%) ANTISEPTIC
● Kills 99.99% of Germs
● Alcohol-Free & Fragrance-Free
● Moisturizing & Soothing
40+ TREATMENTS
COTTON SWABS SOLD SEPARATELY
0.61 FL OZ (18 mL)
DID YOU KNOW?
Most respiratory infections enter through the nose.
NEW PATENTED
NANOTECHNOLOGY
KILLS GERMS THAT ENTER THE NOSE
PROTECTS FOR 8 HOURS*
NEXT-LEVEL PROTECTION AGAINST INFECTION
NanoBio®Protect
Easy to Use.
Simply Shake, Dip & Swab.
NanoBio® is a trademark of BlueWillow Biologics, Inc. All rights reserved.
Distributed by: BlueWillow Biologics, Inc.
Ann Arbor, MI 48105 USA
*Based on ex vivo studies on human skin
ACTUAL SIZE

NDC: 74315-001-01
NanoBio® Protect
Nasal Antiseptic Solution
Benzalkonium Chloride (0.13%) Antiseptic
0.61 FL OZ (18 mL)
Read Drug Facts panel on outer carton before use
Distributed by:
BlueWillow Biologics, Inc.
Ann Arbor, MI 48105 USA